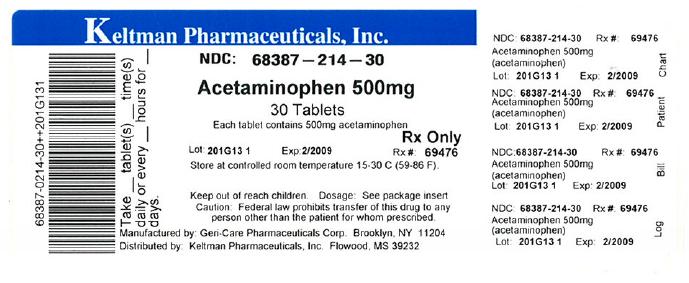 DRUG LABEL: ACETAMINOPHEN
NDC: 68387-214 | Form: TABLET
Manufacturer: Keltman Pharmaceuticals Inc.
Category: otc | Type: HUMAN OTC DRUG LABEL
Date: 20110321

ACTIVE INGREDIENTS: ACETAMINOPHEN 500 mg/1 1
INACTIVE INGREDIENTS: POVIDONE; STARCH, CORN; STEARIC ACID; SODIUM STARCH GLYCOLATE TYPE A POTATO

Acetaminophen Tablet

*Compared to the active ingredient in Extra-Strength Tylenol® Tablets

Drug Facts

ACTIVE INGREDIENT

(in each tablet)

Acetaminophen 500 mg

PURPOSES

Pain Reliever/Fever Reducer

Keep Out of Reach of Children

USES

- temporarily relieves minor aches and pains
- temporarily relieves reduces fever

WARNINGS

Liver warning:

This product contains acetaminophen. Severe liver damage may occur if you take

- more than 8 tablets in 24 hours, which is the maximum daily amount
- with other drugs containing acetaminophen
- 3 or more alcoholic drinks every day while using this product

Do not use

- with any other drug containing acetaminophen (prescription or nonprescription). If you are not sure whether a drug contains acetaminophen, ask a doctor or pharmacist.

Ask a doctor before use if you have liver disease.

Ask a doctor or pharmacist before use if you are taking the blood thinning drug warfarin.

Stop use and ask a doctor if

- pain gets worse or lasts more than 10 days
- fever gets worse or lasts more than 3 days
- new symptoms occur
- redness or swelling is present

These could be signs of a serious condition.

If pregnant or breast-feeding, ask a health professional before use.

Keep out of reach of children.

OVERDOSAGE

Overdose warning:

Taking more than the recommended dose (overdose) may cause liver damage. In case of overdose, get medical help or contact a Poison Control Center right away. Quick medical attention is critical for adults as well as for children even if you do not notice any signs or symptoms.

Directions

Do not take more than directed

Age | Dose
Adults and Children 12 years and over | Take 1-2 tablets every 4-6 hours, as needed. Do not take more than 8 tablets in 24 hours.
Children under 12 years | Do not use.

OTHER INFORMATION

TAMPER EVIDENT: Do not use if imprinted seal under cap is missing or broken.

- store at 20°-25°C (68°-77°F)
- for institutional use only

INACTIVE INGREDIETNS:

povidone, sodium starch glycolate, starch, stearic acid. May also contain: crospovidone, methylparaben and propylparaben

Distributor Information:

*This product is not manufactured or distributed by the owner of the registered trademark TYLENOL®.

Distributed by: GERI-CARE PHARMACEUTICALS CORP. 1650 63rd St., Brooklyn, New York 11204

This Product was Repackaged By Sandhills Packaging For:

Keltman Pharmaceuticals Inc.
1 Lakeland Square, Suite A
Flowood, MS 39232
United States